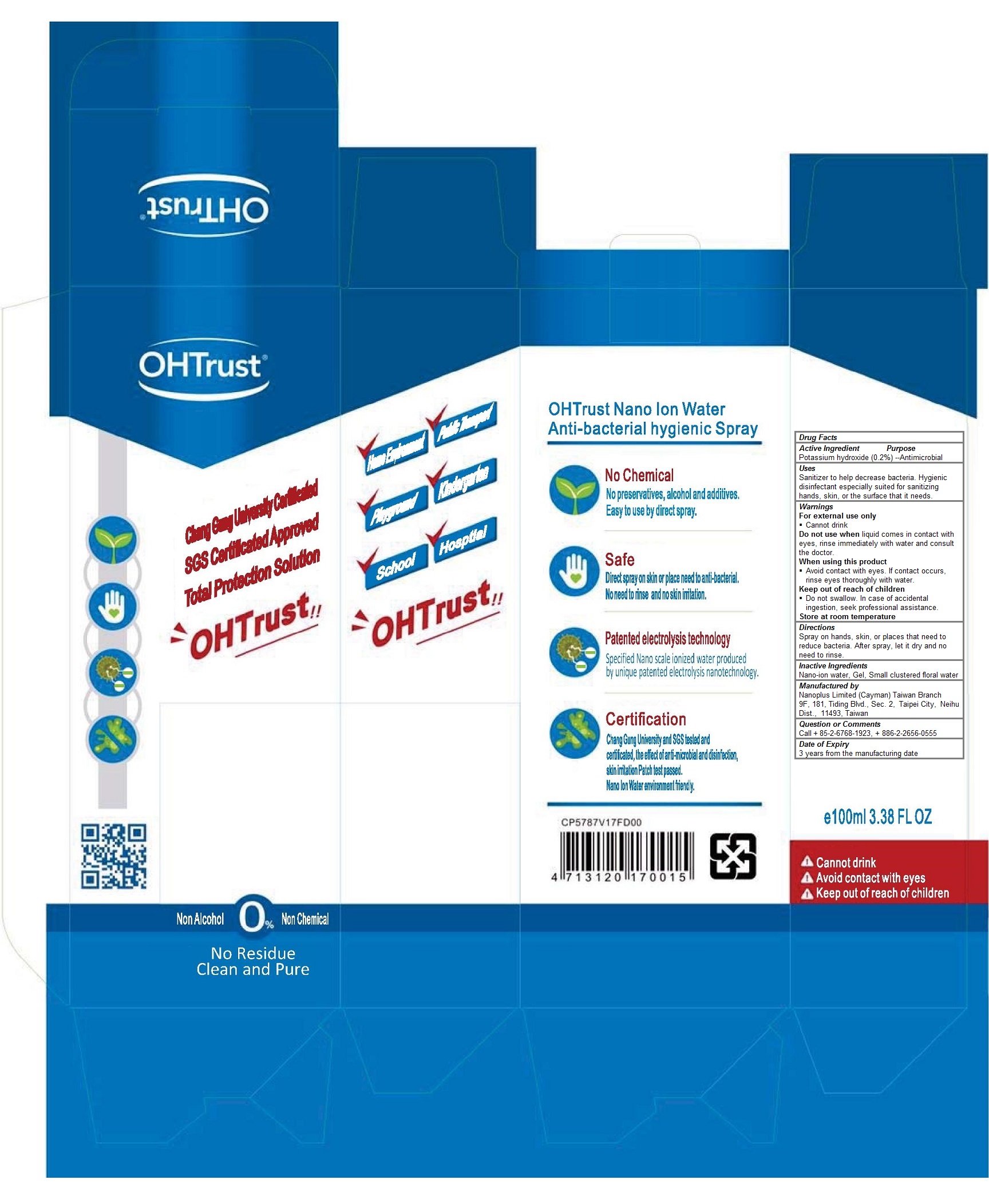 DRUG LABEL: OHTrust Nano Ion Water
NDC: 70970-100 | Form: LIQUID
Manufacturer: Nanoplus Limited (Cayman) Taiwan Branch
Category: otc | Type: HUMAN OTC DRUG LABEL
Date: 20160926

ACTIVE INGREDIENTS: Potassium hydroxide 0.2 g/100 mL
INACTIVE INGREDIENTS: water; GELATIN, UNSPECIFIED

OHTrust Nano Ion Water

Active Ingredients

Potassium hydroxide (0.2%)

Purpose

Antimicrobial

Keep out of reach of children

 Do not swallow. In case of accidental ingestion, seek professional assistance.

Uses

Sanitizer to help decrease bacteria. Hygienic disinfectant especially suited for sanitizing hands, skin, or the surface that it needs.

Warnings

For external use only
 Cannot drink
Do not use when liquid comes in contact with eyes, rinse immediately with water and consult the doctor.
When using this product
 Avoid contact with eyes. If contact occurs, rinse eyes thoroughly with water.

Store at room temperature

Inactive Ingredients

Nano-ion water, Gel, Small clustered floral water

Directions

Spray on hands, skin, or places that need to be antibacterial. After spray, let it dry and no need to rinse.